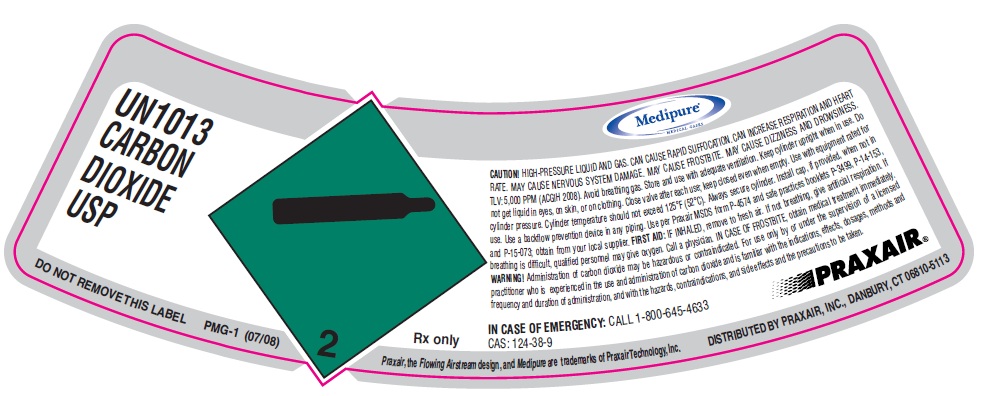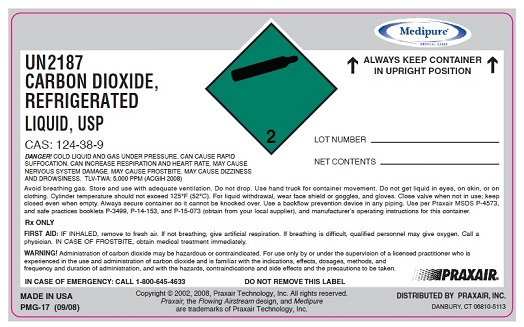 DRUG LABEL: Carbon Dioxide
NDC: 49972-003 | Form: GAS
Manufacturer: Praxair Distribution Southeast LLC
Category: prescription | Type: HUMAN PRESCRIPTION DRUG LABEL
Date: 20121129

ACTIVE INGREDIENTS: Carbon Dioxide 990 mL/1 L

Carbon Dioxide

PACKAGE LABEL

Un1013 CARBON DIOXIDE USP
CONTENTS LOT NUMBER
CAUTION! HIGH-PRESSURE LIQUID AND GAS. CAN CAUSE RAPID SUFFOCATION. CAN INCREASE RESPIRATION AND HEART RATE , MAY CUASE NERVOUS DAMAGE MAY CAUSE FROSTBITE. MAY CAUSEDIZZINESS AND DROWSINESS.
TLV: 5,000 PPM (ACGIH 2008). Avoid breathing gas. Store and use with adequate ventilation. Keep cylinder upright when in use. Do
not get liquid in eyes, on skin, or on clothing. Close valve after each use; keep closed even when empty. Use with equipment rated for
cylinder pressure. Cylinder temperature should not exceed 125°F (52°C). Always secure cylinder. Install cap, if provided, when not in
use. Use a backflow prevention device in any piping. Use per Praxair MSDS form P-4574 and safe practices booklets P-3499, P-14-153,
and P-15-073; obtain from your local supplier. FIRST AID: IF INHALED, remove to fresh air. If not breathing, give artificial respiration. If
breathing is difficult, qualified personnel may give oxygen. Call a physician. IN CASE OF FROSTBITE, obtain medical treatment immediately.
WARNING! Administration of carbon dioxide may be hazardous or contraindicated. For use only by or under the supervision of a licensed
practitioner who is experienced in the use and administration of carbon dioxide and is familiar with the indications, effects, dosages, methods and
frequency and duration of administration, and with the hazards, contraindications, and side effects and the precautions to be taken.
Rx only IN CASE OF EMERGENCY CALL 1-800-645-4633
CAS 124-39-9 DO NOT REMOVE THIS LABEL PMG-1 (07/08)
Praxair, the flowing airstream design and Medipure are trademarks of Praxair Technology, Inc. DISTRIBUTED BY PRAXAIR, INC, DANBURY, CT 06810-5113

PACKAGE LABEL

UN2187
CARBON DIOXIDE,
REFRIGERATED
LIQUID, USP
ALWAYS KEEP CONTAINER
IN UPRIGHT POSITION
LOT NUMBER
NET CONTENTS
DANGER! COLD LIQUID AND GAS UNDER PRESSURE. CAN CAUSE RAPID SUFFOCATION. CAN INCREASE RESPIRATION AND HEART RATE. MAY CAUSE NERVOUS SYSTEM DAMAGE. MAY CAUSE FROSTBITE. MAY CAUSE DIZZINESS AND DROWSINESS. TLV-TWA: 5,000 PPM (ACGIH 2008)
Avoid breathing gas. Store and use with adequate ventilation. Do not drop. Use hand truck for container movement. Do not get liquid in eyes, on skin, or on clothing. Cylinder temperature should not exceed 125°F (52°C). For liquid withdrawal, wear face shield or goggles, and gloves. Close valve when not in use; keep
closed even when empty. Always secure container so it cannot be knocked over. Use a backflow prevention device in any piping. Use per Praxair MSDS P-4573, and safe practices booklets P-3499, P-14-153, and P-15-073 (obtain from your local supplier), and manufacturer’s operating instructions for this container.
Rx ONLY
FIRST AID: IF INHALED, remove to fresh air. If not breathing, give artificial respiration. If breathing is difficult, qualified personnel may give oxygen. Call a physician. IN CASE OF FROSTBITE, obtain medical treatment immediately.
WARNING! Administration of carbon dioxide may be hazardous or contraindicated. For use only by or under the supervision of a licensed practitioner who is experienced in the use and administration of carbon dioxide and is familiar with the indications, effects, dosages, methods, and frequency and duration of administration, and with the hazards, contraindications and side effects and the precautions to be taken.
DO NOT REMOVE THIS LABEL
CAS: 124-38-9
IN CASE OF EMERGENCY: CALL 1-800-645-4633
DO NOT REMOVE THIS LABEL
Rx ONLY CAS 10024-97-2 PRODUCED BY AIR LIQUEFACTION
IN CASE OF EMERGENCY: CALL 1-800-645-4633
DISTRIBUTED BY PRAXAIR, INC., DANBURY
PMG-17 (09/08) MADE IN USA
Copyright @ 2002, 2008. Praxair Technology, Inc. All rights reserved
Praxair, the flowing airstream design and Medipure are trademarks of Praxair Technology, Inc. DISTRIBUTED BY PRAXAIR, INC, DANBURY, CT 06810-5113
DISTRIBUTED BY PRAXAIR, INC., DANBURY